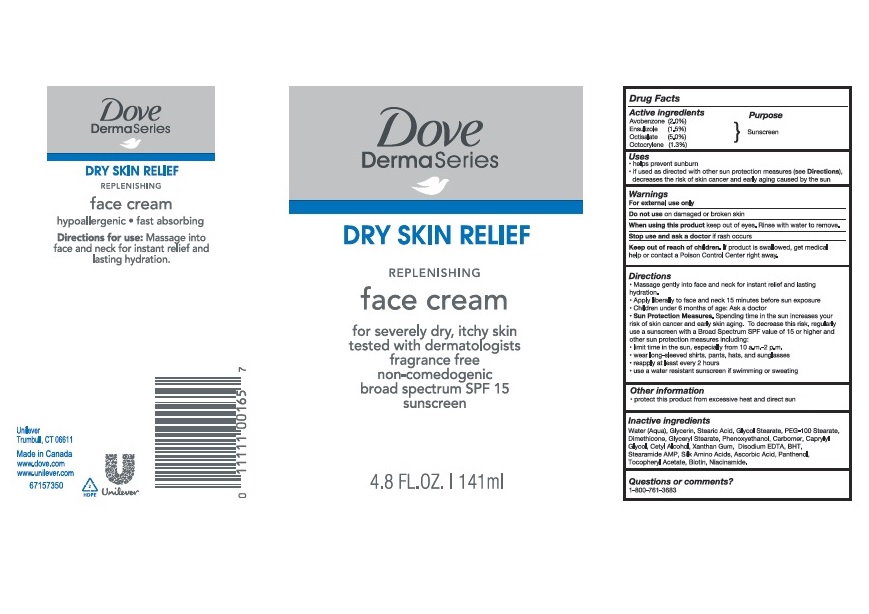 DRUG LABEL: Dove
NDC: 64942-1868 | Form: LOTION
Manufacturer: CONOPCO Inc. d/b/a Unilever
Category: otc | Type: HUMAN OTC DRUG LABEL
Date: 20241107

ACTIVE INGREDIENTS: ENSULIZOLE 1.5 g/100 mL; OCTOCRYLENE 1.3 g/100 mL; OCTISALATE 5 g/100 mL; AVOBENZONE 2 g/100 mL
INACTIVE INGREDIENTS: DIMETHICONE; CARBOMER HOMOPOLYMER, UNSPECIFIED TYPE; GLYCERIN; PEG-100 STEARATE; EDETATE DISODIUM ANHYDROUS; STEARAMIDE AMP; GLYCERYL MONOSTEARATE; PANTHENOL; BIOTIN; STEARIC ACID; PHENOXYETHANOL; BUTYLATED HYDROXYTOLUENE; CAPRYLYL GLYCOL; GLYCOL STEARATE; WATER; NIACINAMIDE; CETYL ALCOHOL; XANTHAN GUM; ASCORBIC ACID; AMINO ACIDS, SILK; .ALPHA.-TOCOPHEROL ACETATE

Dove DermaSeries Dry Skin Relief Replenishing Face Cream Sunscreen SPF 15

Drug Facts

Active ingredient

Avobenzone (2.0%), Ensulizole (1.5%), Octisalate (5%), Octocrylene (1.3%)

Purpose

Sunscreen

Uses

Help prevent sunburn
If used as directed with other sun protection measeures (see Directions) decreases the risk of skin cancer and early skin aging caused by the sun

Warnings

For external use only
Do not use on damaged or broken skin
When using this product keep out of eyes. Rinse with water to remove
Stop use and ask a doctor if rash occurs

Keep out of reach of children
If product is swallowed, get medical help or contact a PoisonCcontrol Center right away.

Directions

Massage gently into face and neck for instant relief and lasting hydration
Apply liberally to face and neck 15 minutes before sun exposure
Children under 6 months of age: Ask a doctor.
Sun Protection Measures Spending time in the sun increases your risk of skin cancer and early skin aging. To decrease this rish, regularly use a sunscreen with a Broad Spectum SPF value of 15 or higher and other sun protection measures including limit time in the sun, especiallu from 10a.m. - 2p.m. wear long-sleeved shirts, pants, hats and sunglasses
Reapply at least every 2 hours
Use a water resistant sunscreen if swimming or sweating

Other information

Protect this product from excessive heat and direct sun

Inactive ingredients

Water (Aqua,. Glycerin, Stearic Acid, Glycol Stearate, PEG-100 Stearate, Dimethicone, Glyceryl Stearate, Phenoxyethanol, Carbomer, Caprylyl Glycol, Xanthan Gum, Disodium EDTA, BHT, Stearamide AMP, Silk Amino Acids, Ascorbic Acid, Panthenol, Tocopheryl Acetate, Biotin, Niacinamide.

Questions or Comments?

1-800-761-3683